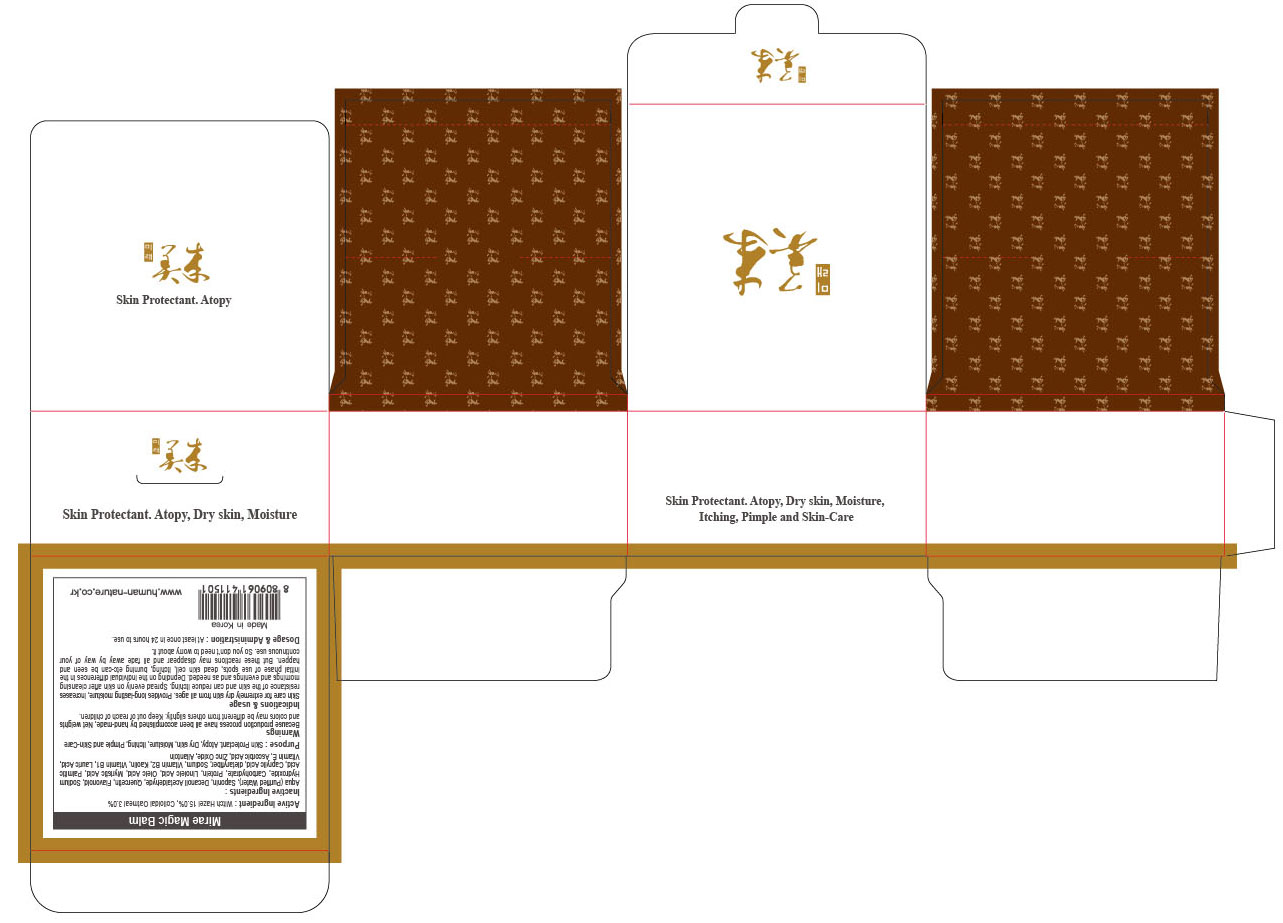 DRUG LABEL: Mirae Magic Balm
NDC: 43071-120 | Form: SOAP
Manufacturer: HUMAN AND NATURE
Category: otc | Type: HUMAN OTC DRUG LABEL
Date: 20191218

ACTIVE INGREDIENTS: Witch Hazel 7.5 g/50 g; Oatmeal 1.5 g/50 g
INACTIVE INGREDIENTS: WATER

ACTIVE INGREDIENT

Active Ingredient: Witch Hazel 15.0%, Colloidal Oatmeal 3.0%

INACTIVE INGREDIENT

Inactive Ingredients: Aqua (Purified Water), Saponin, Decanoil Acetaldehyde, Quercetin, Flavonoid, Sodium Hydroxide, Carbohydrate, Protein, Linoleic Acid, Oleic Acid, Myristic Acid, Palmitic Acid, Caprylic Acid, dietaryfiber, Sodium, Vitamin B2, Kaolin, Vitamin B1, Lauric Acid, Vitamin E, Ascorbic Acid, Zinc Oxide, Allantoin

PURPOSE

Purpose: Skin Protectant. Atopy, Dry skin, Moisture, Itching, Pimple and Skin-Care

WARNINGS

Warnings: Because production process have all been accomplished by hand-made, Net weights and colors may be different from others slightly.

KEEP OUT OF REACH OF CHILDREN

INDICATIONS & USAGE

Indications & usage: Skin care for extremely dry skin from all ages. Provides long-lasting moisture, increases resistance of the skin and can reduce itching. Spread evenly on skin after cleansing mornings and evenings and as needed. Depnding on the individual differences in the initial phase of use spots, dead skin cell, itching, burning etc –can be seen and happen. But these reactions may disappear and all fade away by way of your continuous use. So you don’t need to worry about it.

DOSAGE & ADMINISTRATION

Dosage & Administration: At least once in 24 hours to use.